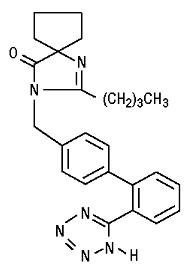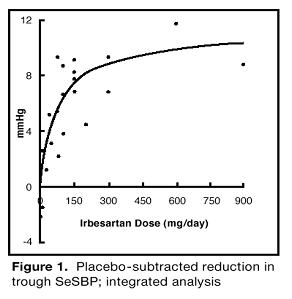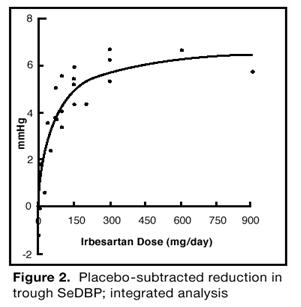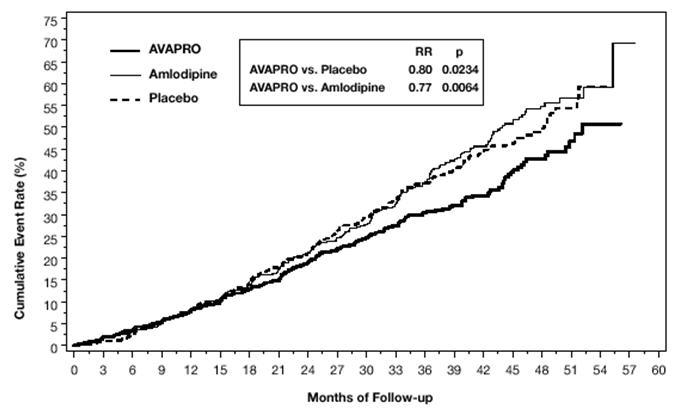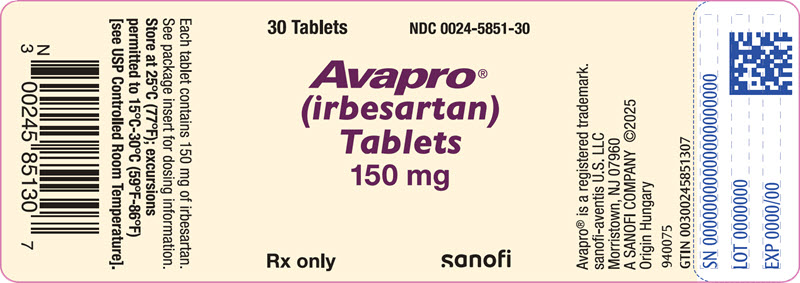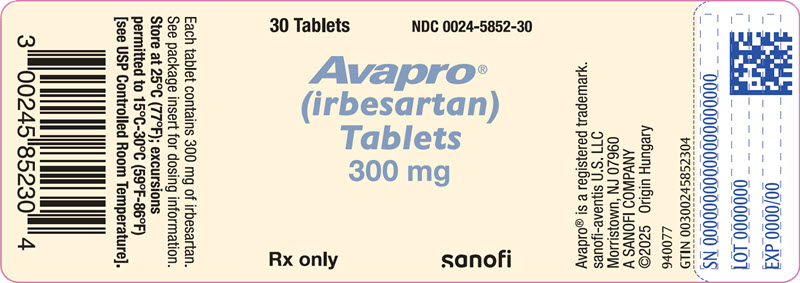 DRUG LABEL: Avapro
NDC: 0024-5851 | Form: TABLET, FILM COATED
Manufacturer: Sanofi-Aventis U.S. LLC
Category: prescription | Type: HUMAN PRESCRIPTION DRUG LABEL
Date: 20260219

ACTIVE INGREDIENTS: IRBESARTAN 150 mg/1 1
INACTIVE INGREDIENTS: LACTOSE MONOHYDRATE; MICROCRYSTALLINE CELLULOSE; CROSCARMELLOSE SODIUM; HYPROMELLOSE, UNSPECIFIED; SILICON DIOXIDE; MAGNESIUM STEARATE; TITANIUM DIOXIDE; POLYETHYLENE GLYCOL 3000; CARNAUBA WAX

HIGHLIGHTS OF PRESCRIBING INFORMATION

These highlights do not include all the information needed to use AVAPRO safely and effectively. See full prescribing information for AVAPRO.
AVAPRO® (irbesartan) tablets, for oral use
Initial U.S. Approval: 1997

WARNING: FETAL TOXICITY

See full prescribing information for complete boxed warning.

- When pregnancy is detected, discontinue AVAPRO as soon as possible. (5.1, 8.1)
- Drugs that act directly on the renin-angiotensin system can cause injury and death to the developing fetus. (5.1, 8.1)

1 INDICATIONS AND USAGE

AVAPRO is an angiotensin II receptor blocker (ARB) indicated for:

- Treatment of hypertension, to lower blood pressure. Lowering blood pressure reduces the risk of fatal and nonfatal cardiovascular events, primarily strokes and myocardial infarctions. (1.1)
- Treatment of diabetic nephropathy in hypertensive patients with type 2 diabetes, an elevated serum creatinine, and proteinuria. (1.2)

2 DOSAGE AND ADMINISTRATION

Indication | Dose
Hypertension (2.2) | 150 to 300 mg once daily
Diabetic Nephropathy (2.3) | 300 mg once daily

3 DOSAGE FORMS AND STRENGTHS

- Tablets: 150 mg, 300 mg (3)

4 CONTRAINDICATIONS

- Hypersensitivity to any component of this product. (4)
- Coadministration with aliskiren in patients with diabetes. (4)

5 WARNINGS AND PRECAUTIONS

- Hypotension: Correct volume or salt depletion prior to administration. (5.2)
- Monitor renal function and serum potassium. (5.3)

6 ADVERSE REACTIONS

- Nephropathy in type 2 diabetic patients: The most common adverse reactions which were more frequent than placebo were hyperkalemia dizziness, orthostatic dizziness, and orthostatic hypotension. (6.1)

To report SUSPECTED ADVERSE REACTIONS, contact sanofi-aventis U.S. LLC at 1-800-633-1610 or FDA at 1-800-FDA-1088 or www.fda.gov/medwatch.

7 DRUG INTERACTIONS

- Lithium: Risk of lithium toxicity. (7)
- Nonsteroidal Anti-inflammatory Drugs (NSAIDs) and COX-2 inhibitors: Increased risk of renal impairment. Reduced antihypertensive effects. (7)
- Dual blockade of the renin-angiotensin system: Increased risk of renal impairment, hypotension, and hyperkalemia. (7)

8 USE IN SPECIFIC POPULATIONS

- Lactation: Potential for adverse effects in infants. (8.2)

FULL PRESCRIBING INFORMATION

WARNING: FETAL TOXICITY

- When pregnancy is detected, discontinue AVAPRO as soon as possible [see Warnings and Precautions (5.1) and Use in Specific Populations (8.1)].
- Drugs that act directly on the renin-angiotensin system can cause injury and death to the developing fetus [see Warnings and Precautions (5.1) and Use in Specific Populations (8.1)].

1 INDICATIONS AND USAGE

1.1 Hypertension

AVAPRO® is indicated for the treatment of hypertension, to lower blood pressure. Lowering blood pressure lowers the risk of fatal and non-fatal cardiovascular (CV) events, primarily strokes and myocardial infarction. These benefits have been seen in controlled trials of antihypertensive drugs from a wide variety of pharmacologic classes including this drug.

Control of high blood pressure should be part of comprehensive cardiovascular risk management, including, as appropriate, lipid control, diabetes management, antithrombotic therapy, smoking cessation, exercise, and limited sodium intake. Many patients will require more than 1 drug to achieve blood pressure goals. For specific advice on goals and management, see published guidelines, such as those of the National High Blood Pressure Education Program's Joint National Committee on Prevention, Detection, Evaluation, and Treatment of High Blood Pressure (JNC).

Numerous antihypertensive drugs, from a variety of pharmacologic classes and with different mechanisms of action, have been shown in randomized controlled trials to reduce cardiovascular morbidity and mortality, and it can be concluded that it is blood pressure reduction, and not some other pharmacologic property of the drugs, that is largely responsible for those benefits. The largest and most consistent cardiovascular outcome benefit has been a reduction in the risk of stroke, but reductions in myocardial infarction and cardiovascular mortality also have been seen regularly.

Elevated systolic or diastolic pressure causes increased cardiovascular risk, and the absolute risk increase per mmHg is greater at higher blood pressures, so that even modest reductions of severe hypertension can provide substantial benefit. Relative risk reduction from blood pressure reduction is similar across populations with varying absolute risk, so the absolute benefit is greater in patients who are at higher risk independent of their hypertension (for example, patients with diabetes or hyperlipidemia), and such patients would be expected to benefit from more aggressive treatment to a lower blood pressure goal.

Some antihypertensive drugs have smaller blood pressure effects (as monotherapy) in black patients, and many antihypertensive drugs have additional approved indications and effects (e.g., on angina, heart failure, or diabetic kidney disease). These considerations may guide selection of therapy.

AVAPRO may be used alone or in combination with other antihypertensive agents.

1.2 Nephropathy in Type 2 Diabetic Patients

AVAPRO is indicated for the treatment of diabetic nephropathy in patients with type 2 diabetes and hypertension, an elevated serum creatinine, and proteinuria (>300 mg/day). In this population, AVAPRO reduces the rate of progression of nephropathy as measured by the occurrence of doubling of serum creatinine or end-stage renal disease (need for dialysis or renal transplantation) [see Clinical Studies (14.2)].

2 DOSAGE AND ADMINISTRATION

2.1 General Considerations

AVAPRO may be administered with other antihypertensive agents and with or without food.

2.2 Hypertension

The recommended initial dose of AVAPRO is 150 mg once daily. The dosage can be increased to a maximum dose of 300 mg once daily as needed to control blood pressure [see Clinical Studies (14.1)].

2.3 Nephropathy in Type 2 Diabetic Patients

The recommended dose is 300 mg once daily [see Clinical Studies (14.2)].

2.4 Dose Adjustment in Volume and Salt-Depleted Patients

The recommended initial dose is 75 mg once daily in patients with depletion of intravascular volume or salt (e.g., patients treated vigorously with diuretics or on hemodialysis) [see Warnings and Precautions (5.2)].

3 DOSAGE FORMS AND STRENGTHS

AVAPRO 150 mg is a white to off-white, biconvex oval, film-coated tablet debossed with a heart on one side and "2872" on the other.

AVAPRO 300 mg is a white to off-white, biconvex oval, film-coated tablet debossed with a heart on one side and "2873" on the other.

4 CONTRAINDICATIONS

AVAPRO is contraindicated in patients who are hypersensitive to any component of this product.

Do not coadminister aliskiren with AVAPRO in patients with diabetes.

5 WARNINGS AND PRECAUTIONS

5.1 Fetal Toxicity

AVAPRO can cause fetal harm when administered to a pregnant woman. Use of drugs that act on the renin-angiotensin system during the second and third trimesters of pregnancy reduces fetal renal function and increases fetal and neonatal morbidity and death. Resulting oligohydramnios can be associated with fetal lung hypoplasia and skeletal deformations. Potential neonatal adverse effects include skull hypoplasia, anuria, hypotension, renal failure, and death. When pregnancy is detected, discontinue AVAPRO as soon as possible [see Use in Specific Populations (8.1)].

5.2 Hypotension in Volume or Salt-Depleted Patients

In patients with an activated renin-angiotensin system, such as volume or salt-depleted patients (e.g., those being treated with high doses of diuretics), symptomatic hypotension may occur after initialization of treatment with AVAPRO. Correct volume or salt depletion prior to administration of AVAPRO or use a lower starting dose [see Dosage and Administration (2.4)].

5.3 Impaired Renal Function

Changes in renal function including acute renal failure can be caused by drugs that inhibit the renin-angiotensin system. Patients whose renal function may depend in part on the activity of the renin-angiotensin system (e.g., patients with renal artery stenosis, chronic kidney disease, severe heart failure, or volume depletion) may be at particular risk of developing acute renal failure or death on AVAPRO. Monitor renal function periodically in these patients. Consider withholding or discontinuing therapy in patients who develop a clinically significant decrease in renal function on AVAPRO [see Drug Interactions (7.3)].

6 ADVERSE REACTIONS

The following important adverse reactions are described elsewhere in the labeling:

- Hypotension in Volume or Salt-Depleted Patients [see Warnings and Precautions (5.2)]
- Impaired Renal Function [see Warnings and Precautions (5.3)]

6.1 Clinical Trials Experience

Because clinical trials are conducted under widely varying conditions, adverse reaction rates observed in the clinical trials of a drug cannot be directly compared to rates in the clinical trials of another drug and may not reflect the rates observed in practice. The adverse reaction information from clinical trials does, however, provide a basis for identifying the adverse events that appear to be related to drug use and for approximating rates.

Hypertension

AVAPRO has been evaluated for safety in more than 4300 patients with hypertension and about 5000 subjects overall. This experience includes 1303 patients treated for over 6 months and 407 patients for 1 year or more.

In placebo-controlled clinical trials, the following adverse reactions were reported in at least 1% of patients treated with AVAPRO (n=1965) and at a higher incidence versus placebo (n=641), excluding those too general to be informative and those not reasonably associated with the use of drug because they were associated with the condition being treated or are very common in the treated population, include: diarrhea (3% vs 2%), dyspepsia/heartburn (2% vs 1%), and fatigue (4% vs 3%).

Irbesartan use was not associated with an increased incidence of dry cough, as is typically associated with ACE inhibitor use. In placebo-controlled studies, the incidence of cough in irbesartan-treated patients was 2.8% versus 2.7% in patients receiving placebo.

Nephropathy in Type 2 Diabetic Patients

Hyperkalemia: In the Irbesartan Diabetic Nephropathy Trial (IDNT) (proteinuria ≥900 mg/day, and serum creatinine ranging from 1.0–3.0 mg/dL), the percent of patients with potassium >6 mEq/L was 18.6% in the AVAPRO group versus 6.0% in the placebo group. Discontinuations due to hyperkalemia in the AVAPRO group were 2.1% versus 0.4% in the placebo group.

In IDNT, the adverse reactions were similar to those seen in patients with hypertension with the exception of an increased incidence of orthostatic symptoms which occurred more frequently in the AVAPRO versus placebo group: dizziness (10.2% vs 6.0%), orthostatic dizziness (5.4% vs 2.7%) and orthostatic hypotension (5.4% vs 3.2%).

6.2 Postmarketing Experience

The following adverse reactions have been identified during postapproval use of AVAPRO. Because these reactions are reported voluntarily from a population of uncertain size, it is not always possible to estimate reliably their frequency or to establish a causal relationship to drug exposure.

Blood and lymphatic system: Anemia, Thrombocytopenia

Ear and labyrinth: Tinnitus

Gastrointestinal: Intestinal angioedema

Hepatobiliary: Hepatitis, Jaundice

Immune system: Anaphylactic reaction including anaphylactic shock

Investigations: Increased liver function tests, Increased CPK (Creatine Phosphokinase)

Metabolism and nutrition: Hyperkalemia, Hypoglycemia in diabetic patients

Skin and subcutaneous tissue: Urticaria, Angioedema (involving swelling of the face, lips, pharynx, and/or tongue)

7 DRUG INTERACTIONS

7.1 Agents Increasing Serum Potassium

Coadministration of AVAPRO with other drugs that raise serum potassium levels may result in hyperkalemia, sometimes severe. Monitor serum potassium in such patients.

7.2 Lithium

Increases in serum lithium concentrations and lithium toxicity have been reported with concomitant use of irbesartan and lithium. Monitor lithium levels in patients receiving irbesartan and lithium.

7.3 Nonsteroidal Anti-inflammatory Drugs (NSAIDs) Including Selective Cyclooxygenase-2 Inhibitors (COX-2 Inhibitors)

In patients who are elderly, volume-depleted (including those on diuretic therapy), or with compromised renal function, coadministration of NSAIDs, including selective COX-2 inhibitors, with angiotensin II receptor antagonists (including irbesartan) may result in deterioration of renal function, including possible acute renal failure. These effects are usually reversible. Monitor renal function periodically in patients receiving irbesartan and NSAID therapy.

The antihypertensive effect of angiotensin II receptor antagonists, including irbesartan, may be attenuated by NSAIDs including selective COX-2 inhibitors.

7.4 Dual Blockade of the Renin-Angiotensin System (RAS)

Dual blockade of the RAS with angiotensin receptor blockers, ACE inhibitors, or aliskiren is associated with increased risks of hypotension, hyperkalemia, and changes in renal function (including acute renal failure) compared to monotherapy. Most patients receiving the combination of two RAS inhibitors do not obtain any additional benefit compared to monotherapy. In general, avoid combined use of RAS inhibitors. Closely monitor blood pressure, renal function and electrolytes in patients on AVAPRO and other agents that affect the RAS.

Do not coadminister aliskiren with AVAPRO in patients with diabetes. Avoid use of aliskiren with AVAPRO in patients with renal impairment (GFR <60 mL/min).

8 USE IN SPECIFIC POPULATIONS

8.1 Pregnancy

Risk Summary

AVAPRO can cause fetal harm when administered to a pregnant woman. Use of drugs that act on the renin-angiotensin system during the second and third trimesters of pregnancy reduces fetal renal function and increases fetal and neonatal morbidity and death [see Clinical Considerations]. Most epidemiologic studies examining fetal abnormalities after exposure to antihypertensive use in the first trimester have not distinguished drugs affecting the renin-angiotensin system from other antihypertensive agents. When pregnancy is detected, discontinue AVAPRO as soon as possible.

All pregnancies have a background risk of birth defect, loss or other adverse outcomes regardless of drug exposure. In the U.S. general population, the estimated background risk of major birth defects and miscarriage in clinically recognized pregnancies is 2% to 4% and 15% to 20%, respectively.

Clinical Considerations

Disease-associated maternal and/or embryo-fetal risk

Hypertension in pregnancy increases the maternal risk for preeclampsia, gestational diabetes, premature delivery, and delivery complications (e.g., need for cesarean section and postpartum hemorrhage). Hypertension increases the fetal risk for intrauterine growth restriction and intrauterine death. Pregnant women with hypertension should be carefully monitored and managed accordingly.

Fetal/neonatal adverse reactions

Oligohydramnios in pregnant women who use drugs affecting the renin-angiotensin system in the second and third trimesters of pregnancy can result in the following: reduced fetal renal function leading to anuria and renal failure, fetal lung hypoplasia, skeletal deformations, including skull hypoplasia, hypotension, and death.

In the unusual case that there is no appropriate alternative to therapy with drugs affecting the renin-angiotensin system for a particular patient, apprise the mother of the potential risk to the fetus.

Perform serial ultrasound examinations to assess the intra-amniotic environment. Fetal testing may be appropriate, based on the week of pregnancy. Patients and physicians should be aware, however, that oligohydramnios may not appear until after the fetus has sustained irreversible injury. If oligohydramnios is observed, consider alternative treatment. Closely observe infants with histories of in utero exposure to AVAPRO for hypotension, oliguria, and hyperkalemia and other symptoms of renal impairment. In neonates with a history of in utero exposure to AVAPRO, if oliguria or hypotension occurs, direct attention toward support of blood pressure and renal perfusion. Exchange transfusion or dialysis may be required as means of reversing hypotension and/or substituting for disordered renal function.

Data

Animal data

Irbesartan crosses the placenta in rats and rabbits. In female rats given irbesartan prior to mating through gestation and lactation at oral doses of 50, 180, or 650 mg/kg/day (1.6 to 21.1 times the maximum recommended human dose (MRHD) based on body surface area), fetuses examined on Gestation Day 20 showed increased incidences of hydroureter and renal pelvic cavitation and/or absence of renal papilla in all irbesartan-treated groups. Subcutaneous edema also occurred in fetuses at maternal doses ≥180 mg/kg/day (5.8 times the MRHD). These anomalies occurred when female rats received irbesartan from prior to mating through Day 20 of gestation but were not observed in pups postnatally in the same study, or when irbesartan was given to pregnant rats only during organogenesis (Gestation Day 6 through Gestation Day 15) at oral doses from 50 to 450 mg/kg/day (up to 14.6 times the MRHD). In addition, no adverse effects on kidney development were observed in pups from dams given irbesartan from Gestation Day 15 through Lactation Day 24 at doses of 50, 180, or 650 mg/kg/day (up to 21.1 times the MRHD). The observed effects are believed to be late gestational effects of the drug. Pregnant rabbits given oral doses of irbesartan of 30 mg/kg/day (1.9 times the MRHD based on body surface area) experienced a high rate of maternal mortality and abortion. Surviving females had a slight increase in early resorptions and a corresponding decrease in live fetuses.

Radioactivity was present in the rat and rabbit fetuses during late gestation following oral doses of radiolabeled irbesartan.

8.2 Lactation

There are no available data on the presence of irbesartan in human milk, effects on milk production, or the breastfed infant. Irbesartan or some metabolite of irbesartan is secreted in the milk of lactating rats [see Clinical Pharmacology (12.3)]. Because of the potential for adverse effects on the nursing infant, the use of AVAPRO in breastfeeding women is not recommended.

8.4 Pediatric Use

Irbesartan, in a study at a dose of up to 4.5 mg/kg/day, once daily, did not appear to lower blood pressure effectively in pediatric patients ages 6 to 16 years.

AVAPRO has not been studied in pediatric patients less than 6 years old.

8.5 Geriatric Use

Of 4925 subjects receiving AVAPRO in controlled clinical studies of hypertension, 911 (18.5%) were 65 years and over, while 150 (3.0%) were 75 years and over. No overall differences in effectiveness or safety were observed between these subjects and younger subjects, but greater sensitivity of some older individuals cannot be ruled out. [See Clinical Pharmacology (12.3) and Clinical Studies (14.1).]

10 OVERDOSAGE

No data are available in regard to overdosage in humans. However, daily doses of 900 mg for 8 weeks were well-tolerated. The most likely manifestations of overdosage are expected to be hypotension and tachycardia; bradycardia might also occur from overdose. Irbesartan is not removed by hemodialysis.

Acute oral toxicity studies with irbesartan in mice and rats indicated acute lethal doses were in excess of 2000 mg/kg, about 25-fold and 50-fold the MRHD (300 mg) based on body surface area, respectively.

11 DESCRIPTION

AVAPRO (irbesartan) is an angiotensin II receptor (AT1 subtype) antagonist.

Irbesartan is a non-peptide compound, chemically described as a 2-butyl-3-[p-(o-1H-tetrazol-5-ylphenyl)benzyl]-1,3-diazaspiro[4.4]non-1-en-4-one.

Its empirical formula is C25H28N6O, and the structural formula:

Irbesartan is a white to off-white crystalline powder with a molecular weight of 428.5. It is a nonpolar compound with a partition coefficient (octanol/water) of 10.1 at pH of 7.4. Irbesartan is slightly soluble in alcohol and methylene chloride and practically insoluble in water.

AVAPRO is available for oral administration in unscored, film-coated tablets containing 150 mg, or 300 mg of irbesartan. Inactive ingredients include: carnauba wax, croscarmellose sodium, hypromellose, lactose monohydrate, magnesium stearate, microcrystalline cellulose, polyethylene glycol, silicon dioxide, and titanium dioxide.

12 CLINICAL PHARMACOLOGY

12.1 Mechanism of Action

Angiotensin II is a potent vasoconstrictor formed from angiotensin I in a reaction catalyzed by angiotensin-converting enzyme (ACE, kininase II). Angiotensin II is the primary vasoactive hormone of the renin-angiotensin system, and an important component in the pathophysiology of hypertension. It also stimulates aldosterone secretion by the adrenal cortex. Irbesartan blocks the vasoconstrictor and aldosterone-secreting effects of angiotensin II by selectively binding to the AT1 angiotensin II receptor found in many tissues (e.g., vascular smooth muscle, adrenal gland). There is also an AT2 receptor in many tissues, but it is not involved in cardiovascular homeostasis.

Irbesartan is a specific competitive antagonist of AT1 receptors with a much greater affinity (more than 8500-fold) for the AT1 receptor than for the AT2 receptor and no agonist activity.

Blockade of the AT1 receptor removes the negative feedback of angiotensin II on renin secretion, but the resulting increased plasma renin activity and circulating angiotensin II do not overcome the effects of irbesartan on blood pressure.

Irbesartan does not inhibit ACE or renin or affect other hormone receptors or ion channels known to be involved in the cardiovascular regulation of blood pressure and sodium homeostasis.

12.2 Pharmacodynamics

In healthy subjects, single oral irbesartan doses of up to 300 mg produced dose-dependent inhibition of the pressor effect of angiotensin II infusions. Inhibition was complete (100%) 4 hours following oral doses of 150 mg or 300 mg and partial inhibition was sustained for 24 hours (60% and 40% at 300 mg and 150 mg, respectively).

In hypertensive patients, angiotensin II receptor inhibition following chronic administration of irbesartan causes a 1.5-fold to 2-fold rise in angiotensin II plasma concentration and a 2-fold to 3-fold increase in plasma renin levels. Aldosterone plasma concentrations generally decline following irbesartan administration, but serum potassium levels are not significantly affected at recommended doses.

In hypertensive patients, chronic oral doses of irbesartan (up to 300 mg) had no effect on glomerular filtration rate, renal plasma flow, or filtration fraction. In multiple dose studies in hypertensive patients, there were no clinically important effects on fasting triglycerides, total cholesterol or HDL-cholesterol concentrations. There was no effect on serum uric acid during chronic oral administration, and no uricosuric effect.

12.3 Pharmacokinetics

Absorption

The oral absorption of irbesartan is rapid and complete with an average absolute bioavailability of 60% to 80%. Following oral administration of AVAPRO, peak plasma concentrations of irbesartan are attained at 1.5 to 2 hours after dosing. Food does not affect the bioavailability of irbesartan.

Irbesartan exhibits linear pharmacokinetics over the therapeutic dose range.

Distribution

Irbesartan is 90% bound to serum proteins (primarily albumin and α1-acid glycoprotein) with negligible binding to cellular components of blood. The average volume of distribution is 53 to 93 liters.

Studies in animals indicate that radiolabeled irbesartan weakly crosses the blood-brain barrier and placenta. Irbesartan is excreted in the milk of lactating rats.

Elimination

Total plasma and renal clearances are in the range of 157 to 176 mL/min and 3.0 to 3.5 mL/min, respectively. The terminal elimination half-life of irbesartan averages 11 to 15 hours. Steady-state concentrations are achieved within 3 days. Limited accumulation of irbesartan (<20%) is observed in plasma upon repeated once-daily dosing and is not clinically relevant.

Metabolism

Irbesartan is an orally active agent that does not require biotransformation into an active form. Irbesartan is metabolized via glucuronide conjugation and oxidation. Following oral or intravenous administration of ^14C-labeled irbesartan, more than 80% of the circulating plasma radioactivity is attributable to unchanged irbesartan. The primary circulating metabolite is the inactive irbesartan glucuronide conjugate (approximately 6%). The remaining oxidative metabolites do not add appreciably to irbesartan's pharmacologic activity.

In vitro studies indicate irbesartan is oxidized primarily by CYP2C9; metabolism by CYP3A4 is negligible.

Excretion

Irbesartan and its metabolites are excreted by both biliary and renal routes. Following either oral or intravenous administration of ^14C-labeled irbesartan, about 20% of radioactivity is recovered in the urine and the remainder in the feces, as irbesartan or irbesartan glucuronide.

Specific Populations

Sex

No sex-related differences in pharmacokinetics are observed in healthy elderly (age 65–80 years) or in healthy young (age 18–40 years) subjects. In studies of hypertensive patients, there is no sex difference in half-life or accumulation, but somewhat higher plasma concentrations of irbesartan are observed in females (11%–44%). No sex-related dosage adjustment is necessary.

Geriatrics

In elderly subjects (age 65–80 years), irbesartan elimination half-life is not significantly altered, but AUC and Cmax values are about 20% to 50% greater than those of young subjects (age 18–40 years). No dosage adjustment is necessary in the elderly.

Race/ethnicity

In healthy black subjects, irbesartan AUC values are approximately 25% greater than whites; there is no difference in Cmax values.

Renal impairment

The pharmacokinetics of irbesartan is not altered in patients with renal impairment or in patients on hemodialysis. Irbesartan is not removed by hemodialysis. No dosage adjustment is necessary in patients with mild to severe renal impairment unless a patient with renal impairment is also volume depleted [see Warnings and Precautions (5.2) and Dosage and Administration (2.4)].

Hepatic insufficiency

The pharmacokinetics of irbesartan following repeated oral administration are not significantly affected in patients with mild to moderate cirrhosis of the liver. No dosage adjustment is necessary in patients with hepatic insufficiency.

Drug-Drug Interactions

In vitro studies show significant inhibition of the formation of oxidized irbesartan metabolites with the known cytochrome CYP2C9 substrates/inhibitors sulphenazole, tolbutamide and nifedipine. However, in clinical studies the consequences of concomitant irbesartan on the pharmacodynamics of warfarin were negligible. Based on in vitro data, no interaction would be expected with drugs whose metabolism is dependent upon cytochrome P450 isoenzymes 1A1, 1A2, 2A6, 2B6, 2D6, 2E1, or 3A4.

In separate studies of patients receiving maintenance doses of warfarin, hydrochlorothiazide, or digoxin, irbesartan administration for 7 days has no effect on the pharmacodynamics of warfarin (prothrombin time) or pharmacokinetics of digoxin. The pharmacokinetics of irbesartan are not affected by coadministration of nifedipine or hydrochlorothiazide.

13 NONCLINICAL TOXICOLOGY

13.1 Carcinogenesis, Mutagenesis, Impairment of Fertility

No evidence of carcinogenicity was observed when irbesartan was administered at dosages of up to 500/1000 mg/kg/day (males/females, respectively) in rats and 1000 mg/kg/day in mice for up to 2 years. For male and female rats, 500 mg/kg/day provided an average systemic exposure to irbesartan (AUC0–24 hour, bound plus unbound) about 3 and 11 times, respectively, the average systemic exposure in humans receiving the maximum recommended human dose (MRHD) of 300 mg irbesartan/day, whereas 1000 mg/kg/day (administered to females only) provided an average systemic exposure about 21 times that reported for humans at the MRHD. For male and female mice, 1000 mg/kg/day provided an exposure to irbesartan about 3 and 5 times, respectively, the human exposure at 300 mg/day.

Irbesartan was not mutagenic in a battery of in vitro tests (Ames microbial test, rat hepatocyte DNA repair test, V79 mammalian-cell forward gene-mutation assay). Irbesartan was negative in several tests for induction of chromosomal aberrations (in vitro—human lymphocyte assay; in vivo—mouse micronucleus study).

Irbesartan had no adverse effects on fertility or mating of male or female rats at oral dosages ≤650 mg/kg/day, the highest dose providing a systemic exposure to irbesartan (AUC0–24 hour, bound plus unbound) about 5 times that found in humans receiving the MRHD of 300 mg/day.

14 CLINICAL STUDIES

14.1 Hypertension

The antihypertensive effects of AVAPRO were examined in 7 placebo-controlled 8- to 12-week trials in patients with baseline diastolic blood pressures of 95 to 110 mmHg. Doses of 1 to 900 mg were included in these trials in order to fully explore the dose-range of irbesartan. These studies allowed comparison of once or twice-daily regimens at 150 mg/day, comparisons of peak and trough effects, and comparisons of response by sex, age, and race. Two of the seven placebo-controlled trials identified above examined the antihypertensive effects of irbesartan and hydrochlorothiazide in combination.

The 7 studies of irbesartan monotherapy included a total of 1915 patients randomized to irbesartan (1–900 mg) and 611 patients randomized to placebo. Once-daily doses of 150 mg and 300 mg provided statistically and clinically significant decreases in systolic and diastolic blood pressure with trough (24 hours post-dose) effects after 6 to 12 weeks of treatment compared to placebo, of about 8–10/5–6 mmHg and 8–12/5–8 mmHg, respectively. No further increase in effect was seen at dosages greater than 300 mg. The dose-response relationships for effects on systolic and diastolic pressure are shown in Figures 1 and 2.

Once-daily administration of therapeutic doses of irbesartan gave peak effects at around 3 to 6 hours and, in one ambulatory blood pressure monitoring study, again around 14 hours. This was seen with both once-daily and twice-daily dosing. Trough-to-peak ratios for systolic and diastolic response were generally between 60% and 70%. In a continuous ambulatory blood pressure monitoring study, once-daily dosing with 150 mg gave trough and mean 24-hour responses similar to those observed in patients receiving twice-daily dosing at the same total daily dose.

In controlled trials, the addition of irbesartan to hydrochlorothiazide doses of 6.25 mg, 12.5 mg, or 25 mg produced further dose-related reductions in blood pressure similar to those achieved with the same monotherapy dose of irbesartan. HCTZ also had an approximately additive effect.

Analysis of age, sex, and race subgroups of patients showed that men and women, and patients over and under 65 years of age, had generally similar responses. Irbesartan was effective in reducing blood pressure regardless of race, although the effect was somewhat less in blacks (usually a low-renin population).

The effect of irbesartan is apparent after the first dose, and it is close to its full observed effect at 2 weeks. At the end of an 8-week exposure, about 2/3 of the antihypertensive effect was still present one week after the last dose. Rebound hypertension was not observed. There was essentially no change in average heart rate in irbesartan-treated patients in controlled trials.

14.2 Nephropathy in Type 2 Diabetic Patients

The Irbesartan Diabetic Nephropathy Trial (IDNT) was a randomized, placebo- and active-controlled, double-blind, multicenter study conducted worldwide in 1715 patients with type 2 diabetes, hypertension (SeSBP >135 mmHg or SeDBP >85 mmHg), and nephropathy (serum creatinine 1.0 to 3.0 mg/dL in females or 1.2 to 3.0 mg/dL in males and proteinuria ≥900 mg/day). Patients were randomized to receive AVAPRO 75 mg, amlodipine 2.5 mg, or matching placebo once-daily. Patients were titrated to a maintenance dose of AVAPRO 300 mg, or amlodipine 10 mg, as tolerated. Additional antihypertensive agents (excluding ACE inhibitors, angiotensin II receptor antagonists and calcium channel blockers) were added as needed to achieve blood pressure goal (≤135/85 or 10 mmHg reduction in systolic blood pressure if higher than 160 mmHg) for patients in all groups.

The study population was 66.5% male, 72.9% below 65 years of age, and 72% White (Asian/Pacific Islander 5.0%, Black 13.3%, Hispanic 4.8%). The mean baseline seated systolic and diastolic blood pressures were 159 mmHg and 87 mmHg, respectively. The patients entered the trial with a mean serum creatinine of 1.7 mg/dL and mean proteinuria of 4144 mg/day.

The mean blood pressure achieved was 142/77 mmHg for AVAPRO, 142/76 mmHg for amlodipine, and 145/79 mmHg for placebo. Overall, 83.0% of patients received the target dose of irbesartan more than 50% of the time. Patients were followed for a mean duration of 2.6 years.

The primary composite endpoint was the time to occurrence of any one of the following events: doubling of baseline serum creatinine, end-stage renal disease (ESRD; defined by serum creatinine ≥6 mg/dL, dialysis, or renal transplantation), or death. Treatment with AVAPRO resulted in a 20% risk reduction versus placebo (p=0.0234) (see Figure 3 and Table 1). Treatment with AVAPRO also reduced the occurrence of sustained doubling of serum creatinine as a separate endpoint (33%), but had no significant effect on ESRD alone and no effect on overall mortality (see Table 1).

Figure 3: IDNT: Kaplan-Meier Estimates of Primary Endpoint (Doubling of Serum Creatinine, End-Stage Renal Disease or All-Cause Mortality)

The percentages of patients experiencing an event during the course of the study can be seen in Table 1 below:

Table 1: IDNT: Components of Primary Composite Endpoint
 |  | Comparison with Placebo |  |  | Comparison with Amlodipine
 | AVAPRO N=579 (%) | Placebo N=569 (%) | Hazard Ratio | 95% CI | Amlodipine N=567 (%) | Hazard Ratio | 95% CI
Primary Composite Endpoint | 32.6 | 39.0 | 0.80 | 0.66–0.97 (p=0.0234) | 41.1 | 0.77 | 0.63–0.93
Breakdown of first occurring event contributing to primary endpoint
2× creatinine | 14.2 | 19.5 | --- | --- | 22.8 | --- | ---
ESRD | 7.4 | 8.3 | --- | --- | 8.8 | --- | ---
Death | 11.1 | 11.2 | --- | --- | 9.5 | --- | ---
Incidence of total events over entire period of follow-up
2× creatinine | 16.9 | 23.7 | 0.67 | 0.52–0.87 | 25.4 | 0.63 | 0.49–0.81
ESRD | 14.2 | 17.8 | 0.77 | 0.57–1.03 | 18.3 | 0.77 | 0.57–1.03
Death | 15.0 | 16.3 | 0.92 | 0.69–1.23 | 14.6 | 1.04 | 0.77–1.40

The secondary endpoint of the study was a composite of cardiovascular mortality and morbidity (myocardial infarction, hospitalization for heart failure, stroke with permanent neurological deficit, amputation). There were no statistically significant differences among treatment groups in these endpoints. Compared with placebo, AVAPRO significantly reduced proteinuria by about 27%, an effect that was evident within 3 months of starting therapy. AVAPRO significantly reduced the rate of loss of renal function (glomerular filtration rate), as measured by the reciprocal of the serum creatinine concentration, by 18.2%.

Table 2 presents results for demographic subgroups. Subgroup analyses are difficult to interpret, and it is not known whether these observations represent true differences or chance effects. For the primary endpoint, AVAPRO's favorable effects were seen in patients also taking other antihypertensive medications (angiotensin II receptor antagonists, angiotensin-converting-enzyme inhibitors, and calcium channel blockers were not allowed), oral hypoglycemic agents, and lipid-lowering agents.

Table 2: IDNT: Primary Efficacy Outcome within Subgroups
Baseline Factors | AVAPRO N=579 (%) | Comparison with Placebo
Baseline Factors | AVAPRO N=579 (%) | Placebo N=569 (%) | Hazard Ratio | 95% Cl
Sex
Male | 27.5 | 36.7 | 0.68 | 0.53–0.88
Female | 42.3 | 44.6 | 0.98 | 0.72–1.34
Race
White | 29.5 | 37.3 | 0.75 | 0.60–0.95
Non-White | 42.6 | 43.5 | 0.95 | 0.67–1.34
Age (years)
<65 | 31.8 | 39.9 | 0.77 | 0.62–0.97
≥65 | 35.1 | 36.8 | 0.88 | 0.61–1.29

16 HOW SUPPLIED/STORAGE AND HANDLING

AVAPRO (irbesartan) is available as white to off-white, biconvex oval, film-coated tablets, debossed with a heart shape on one side and a code on the other (see Table below). Unit-of-use bottles contain 30 film-coated tablets as follows:

 | 150 mg | 300 mg
Debossing | 2872 | 2873
Bottle of 30 | 0024-5851-30 | 0024-5852-30

STORAGE AND HANDLING

Store at 25°C (77°F); excursions permitted to 15°C–30°C (59°F–86°F) [see USP Controlled Room Temperature].

17 PATIENT COUNSELING INFORMATION

Pregnancy

Advise female patients of childbearing age about the consequences of exposure to AVAPRO during pregnancy. Discuss treatment options with women planning to become pregnant. Patients should be asked to report pregnancies to their physicians as soon as possible.

Potassium Supplements

Advise patients receiving AVAPRO not to use potassium supplements or salt substitutes containing potassium without consulting their healthcare provider [see Drug Interactions (7.1)].

sanofi-aventis U.S. LLC
Morristown, NJ 07960
A SANOFI COMPANY

©202X sanofi-aventis U.S. LLC

PRINCIPAL DISPLAY PANEL - 150 mg Tablet Bottle Label

30 Tablets

NDC 0024-5851-30

Avapro®
(irbesartan)
Tablets
150 mg

Rx only

sanofi

PRINCIPAL DISPLAY PANEL - 300 mg Tablet Bottle Label

30 Tablets

NDC 0024-5852-30

Avapro®
(irbesartan)
Tablets
300 mg

Rx only

sanofi